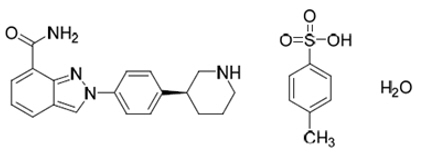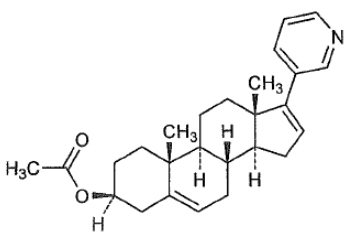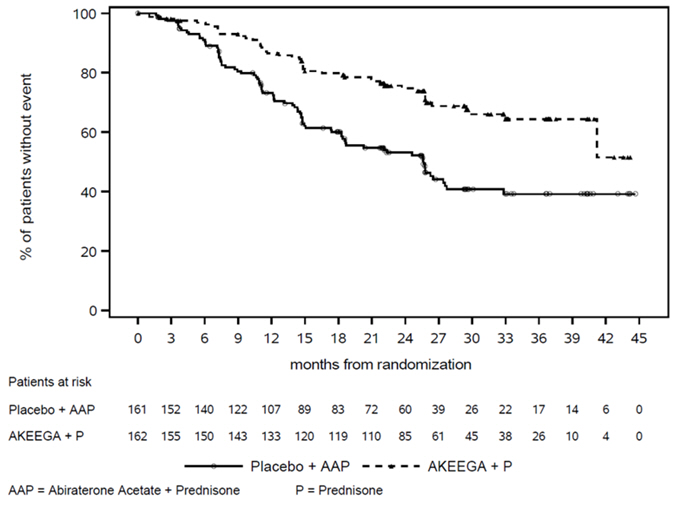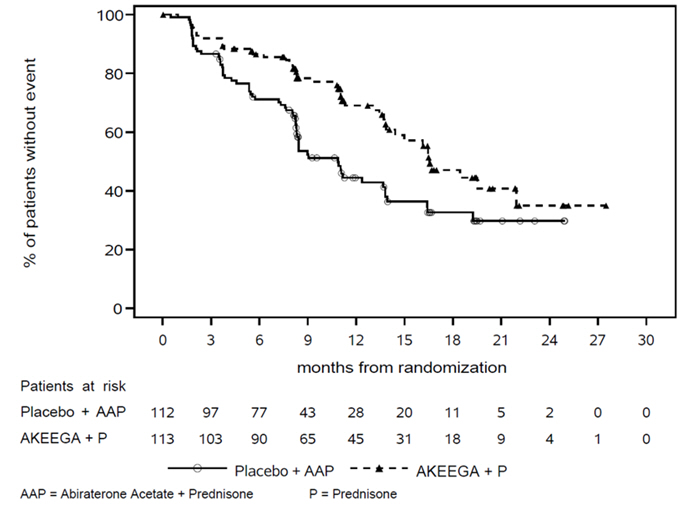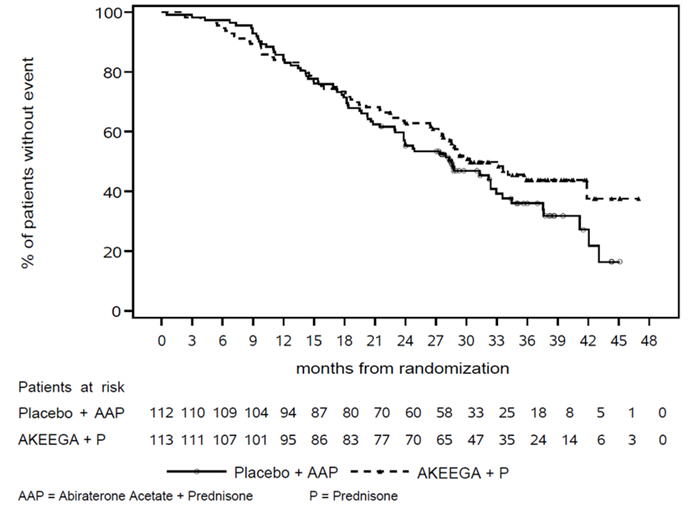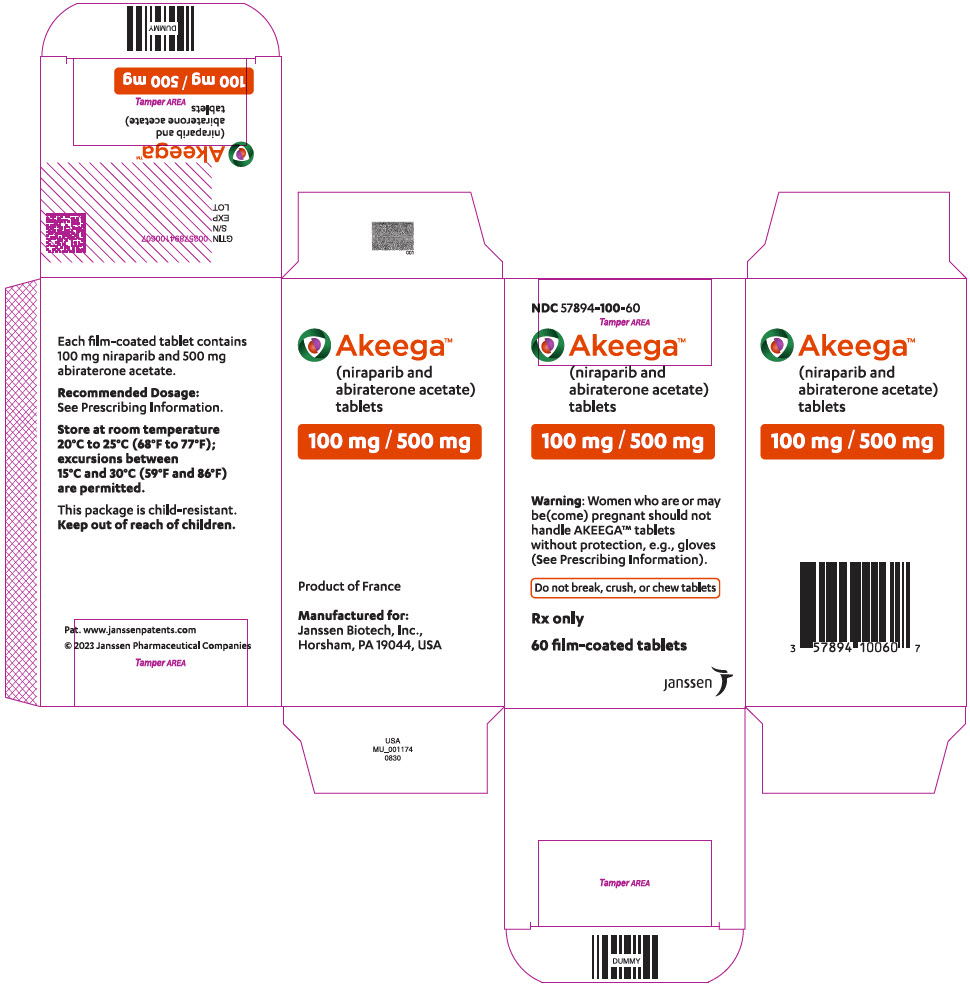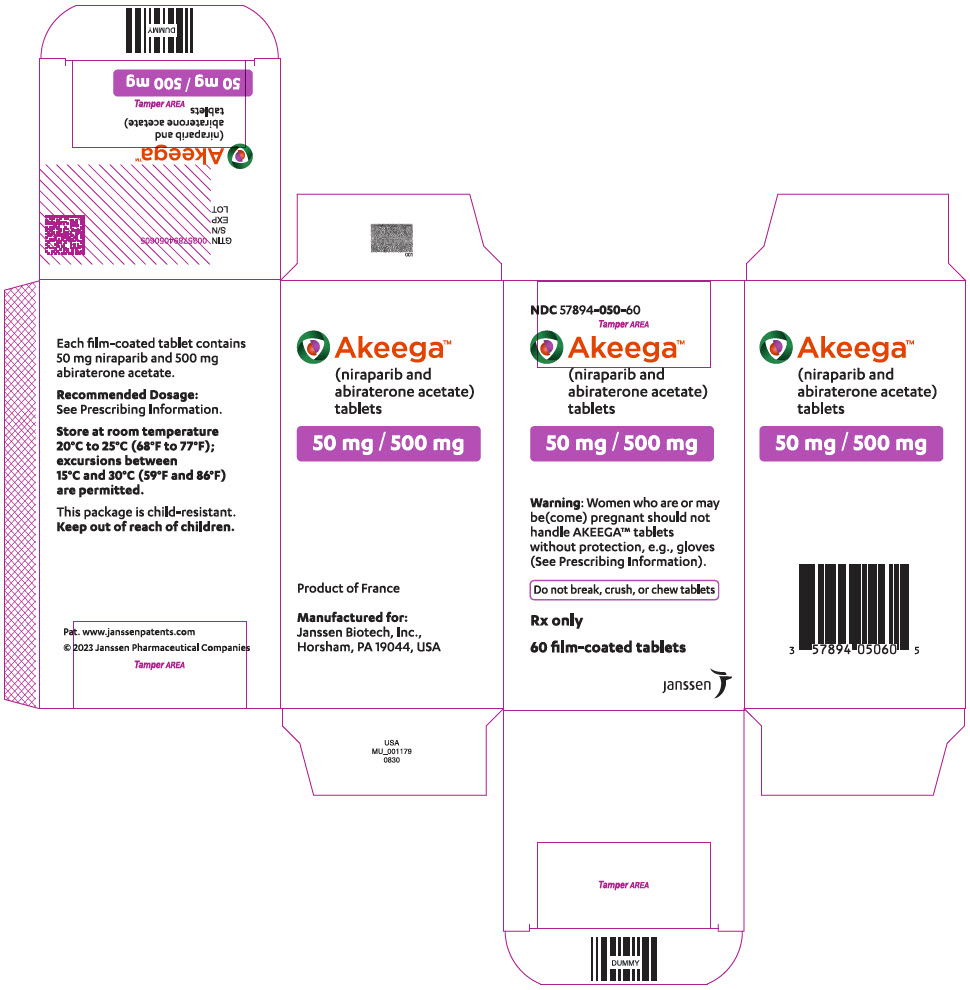 DRUG LABEL: AKEEGA
NDC: 57894-100 | Form: TABLET, FILM COATED
Manufacturer: Janssen Biotech, Inc.
Category: prescription | Type: HUMAN PRESCRIPTION DRUG LABEL
Date: 20251218

ACTIVE INGREDIENTS: NIRAPARIB TOSYLATE MONOHYDRATE 100 mg/1 1; ABIRATERONE ACETATE 500 mg/1 1
INACTIVE INGREDIENTS: SILICON DIOXIDE; CROSPOVIDONE, UNSPECIFIED; HYPROMELLOSE, UNSPECIFIED; LACTOSE MONOHYDRATE; MAGNESIUM STEARATE; MICROCRYSTALLINE CELLULOSE; SODIUM LAURYL SULFATE; FERRIC OXIDE RED; FERRIC OXIDE YELLOW; GLYCERYL MONOCAPRYLOCAPRATE; POLYVINYL ALCOHOL, UNSPECIFIED; TALC; TITANIUM DIOXIDE

HIGHLIGHTS OF PRESCRIBING INFORMATION

These highlights do not include all the information needed to use AKEEGA safely and effectively. See full prescribing information for AKEEGA.
AKEEGA® (niraparib and abiraterone acetate) tablets, for oral use
Initial U.S. Approval: 2023

RECENT MAJOR CHANGES

Indications and Usage (1) | 12/2025
Dosage and Administration (2.1, 2.2) | 12/2025
Warnings and Precautions (5.1, 5.2, 5.3, 5.4) | 12/2025

1 INDICATIONS AND USAGE

AKEEGA is a combination of niraparib, a poly (ADP-ribose) polymerase (PARP) inhibitor, and abiraterone acetate, a CYP17 inhibitor indicated with prednisone for the treatment of adult patients with:

- deleterious or suspected deleterious BRCA2-mutated (BRCA2m) metastatic castration-sensitive prostate cancer (mCSPC).
- deleterious or suspected deleterious BRCA-mutated (BRCAm) metastatic castration-resistant prostate cancer (mCRPC).
- Select patients for therapy based on an FDA-approved test for AKEEGA. (1, 2.1)

2 DOSAGE AND ADMINISTRATION

BRCA2m mCSPC:

- The recommended dosage of AKEEGA is 200 mg niraparib/1,000 mg abiraterone acetate orally once daily in combination with 5 mg prednisone daily until disease progression or unacceptable toxicity. (2.2)

BRCAm mCRPC :

- The recommended dosage of AKEEGA is 200 mg niraparib/1,000 mg abiraterone acetate orally once daily in combination with 10 mg prednisone daily until disease progression or unacceptable toxicity. (2.2)
- Patients receiving AKEEGA should also receive a gonadotropin-releasing hormone (GnRH) analog concurrently or should have had bilateral orchiectomy. (2.2)
- Take AKEEGA on an empty stomach at least one hour before or two hours after food. (2.2)
- For adverse reactions, consider interruption of treatment, dose reduction, or dose discontinuation. (2.3)

3 DOSAGE FORMS AND STRENGTHS

Tablets:

- 50 mg niraparib/500 mg abiraterone acetate (3)
- 100 mg niraparib/500 mg abiraterone acetate (3)

4 CONTRAINDICATIONS

None. (4)

5 WARNINGS AND PRECAUTIONS

- Myelodysplastic Syndrome/Acute Myeloid Leukemia (MDS/AML): MDS/AML, including a case with fatal outcome, has been observed in patients treated with AKEEGA. Monitor patients for hematological toxicity and discontinue if MDS/AML is confirmed. (5.1)
- Myelosuppression:Test complete blood counts weekly for the first month, every two weeks for the next two months, monthly for the remainder of the first year, then every other month, and as clinically indicated. (2.3, 5.2)
- Hypokalemia, Fluid Retention, and Cardiovascular Adverse Reactions:Monitor patients for hypertension, hypokalemia, and fluid retention at least weekly for the first two months, then once a month. Closely monitor patients whose underlying medical conditions might be compromised by increases in blood pressure, hypokalemia, or fluid retention. Control hypertension and correct hypokalemia before and during treatment with AKEEGA. (5.3)
- Hepatotoxicity:Can be severe and fatal. Monitor liver function and modify, interrupt, or discontinue treatment as recommended. (2.3, 5.4)
- Adrenocortical insufficiency: Monitor for symptoms and signs of adrenocortical insufficiency. Increased dosage of corticosteroids may be indicated before, during and after stressful situations. (5.5)
- Hypoglycemia:Severe hypoglycemia has been reported when abiraterone acetate, a component of AKEEGA, was administered to patients receiving medications containing thiazolidinediones (including pioglitazone) or repaglinide. Monitor blood glucose in patients with diabetes during and assess if antidiabetic agent dose modifications are required. (5.6)
- Increased fractures and mortality in combination with radium Ra 223 dichloride: Use of AKEEGA plus prednisone in combination with radium Ra 223 dichloride is not recommended. (5.7)
- Posterior Reversible Encephalopathy Syndrome (PRES):PRES has been observed in patients treated with niraparib, a component of AKEEGA. Discontinue AKEEGA if PRES is confirmed. (5.8)
- Embryo-Fetal Toxicity:AKEEGA can cause fetal harm. Advise males with female partners of reproductive potential to use effective contraception. (5.9, 8.1, 8.3)

6 ADVERSE REACTIONS

- The most common adverse reactions (≥20%), including laboratory abnormalities, are decreased hemoglobin, decreased lymphocytes, musculoskeletal pain, fatigue, decreased platelets, increased alkaline phosphatase, constipation, hypertension, nausea, decreased neutrophils, increased creatinine, increased potassium, decreased potassium, increased AST, fluid retention/edema, increased bilirubin, respiratory tract infection and arrhythmia. (6)

To report SUSPECTED ADVERSE REACTIONS, contact Janssen Biotech, Inc. at 1-800-526-7736 (1-800-JANSSEN) or FDA at 1-800-FDA-1088 or www.fda.gov/medwatch.

7 DRUG INTERACTIONS

- Strong CYP3A4 Inducers: Avoid coadministration. (7.1)
- CYP2D6 Substrates: Avoid coadministration of AKEEGA with CYP2D6 substrates for which minimal changes in concentration may lead to serious toxicities. If alternative treatments cannot be used, consider a dose reduction of the concomitant CYP2D6 substrate. (7.2)

8 USE IN SPECIFIC POPULATIONS

- Moderate or Severe Hepatic impairment: Avoid use. (8.6)

FULL PRESCRIBING INFORMATION

1 INDICATIONS AND USAGE

AKEEGA with prednisone is indicated for the treatment of adult patients with deleterious or suspected deleterious BRCA2-mutated (BRCA2m) metastatic castration-sensitive prostate cancer (mCSPC).

AKEEGA with prednisone is indicated for the treatment of adult patients with deleterious or suspected deleterious BRCA-mutated (BRCAm) metastatic castration-resistant prostate cancer (mCRPC).

Select patients for therapy based on an FDA-approved test for AKEEGA [see Dosage and Administration (2.1)] .

2 DOSAGE AND ADMINISTRATION

2.1 Patient Selection

Select patients for the treatment of mCSPC with AKEEGA based on the presence of a BRCA2 gene alteration [see Clinical Studies (14.1)] .

Select patients for the treatment of mCRPC with AKEEGA based on the presence of a BRCA gene alteration [see Clinical Studies (14.2)] .

Information on FDA-approved tests is available at: http://www.fda.gov/CompanionDiagnostics.

2.2 Recommended Dosage

BRCA2-mutated (BRCA2m) Metastatic Castration-Sensitive Prostate Cancer (mCSPC)

- The recommended dosage of AKEEGA is 200 mg niraparib/1,000 mg abiraterone acetate orally once daily in combination with 5 mg prednisone once daily until disease progression or unacceptable toxicity.

BRCA-mutated (BRCAm) Metastatic Castration-Resistant Prostate Cancer (mCRPC)

- The recommended dosage of AKEEGA is 200 mg niraparib/1,000 mg abiraterone acetate orally once daily in combination with 10 mg prednisone once daily until disease progression or unacceptable toxicity.

Patients receiving AKEEGA should also receive a gonadotropin-releasing hormone (GnRH) analog concurrently or should have had bilateral orchiectomy.

Take AKEEGA on an empty stomach at least one hour before or two hours after food. Swallow tablets whole with water. Do not break, crush, or chew tablets.

If a patient misses a dose, instruct patients to take the dose as soon as possible on the same day and resume their next dose at the normal schedule the following day.

2.3 Dosage Modification for Adverse Reactions

The recommended dosage modifications for AKEEGA are provided in Table 1.

Treatment with AKEEGA should not be reinitiated until the toxicity has resolved to Grade 1 or baseline. If the toxicity is attributed to one component of AKEEGA, the other component of AKEEGA may be continued as a single agent at the current dose until the adverse reaction resolves and AKEEGA can be resumed (see Table 1).

Table 1: Dosage Modifications for Adverse Reactions
Adverse Reaction | Severity | Dosage Modification
Myelosuppression [see Warnings and Precautions (5.2)] | Hemoglobin <8 g/dL | - Withhold AKEEGA and monitor blood counts weekly. - When hemoglobin returns to ≥9 g/dL, resume at the reduced dose of AKEEGA 100 mg/1,000 mg once daily and monitor blood counts weekly for 28 days and as clinically indicated. - Permanently discontinue AKEEGA if hemoglobin has not returned to acceptable levels within 28 days of the dose interruption period or if the patient has already undergone dose reduction to 100 mg/1,000 mg once daily. [If myelodysplastic syndrome or acute myeloid leukemia (MDS/AML) is confirmed, discontinue AKEEGA [see Warnings and Precautions (5.1)].]
Myelosuppression [see Warnings and Precautions (5.2)] | Platelet count <100,000/mcL | First occurrence:; - Withhold AKEEGA for a maximum of 28 days and monitor blood counts weekly until platelet counts return to ≥100,000/mcL. - Resume AKEEGA at same or the reduced dose of 100 mg/1,000 mg once daily. - If platelet count is <75,000/mcL, resume at the reduced dose of AKEEGA 100 mg/1,000 mg once daily.; Second occurrence:; - Withhold AKEEGA for a maximum of 28 days and monitor blood counts weekly until platelet counts return to ≥100,000/mcL. - Resume at the reduced dose of AKEEGA 100 mg/1,000 mg once daily. - Permanently discontinue AKEEGA if the platelet count has not returned to acceptable levels within 28 days of the dose interruption period or if the patient has already undergone dose reduction to 100 mg/1,000 mg once daily.
Myelosuppression [see Warnings and Precautions (5.2)] | Neutrophil <1,000/mcL | - Withhold AKEEGA and monitor blood counts weekly. - When neutrophil counts return to ≥1,500/mcL, resume at the reduced dose of AKEEGA 100 mg/1,000 mg once daily and monitor blood counts weekly for 28 days and as clinically indicated. - Permanently discontinue AKEEGA if neutrophils have not returned to acceptable levels within 28 days of the dose interruption period or if the patient has already undergone dose reduction to 100 mg/1,000 mg once daily.
Myelosuppression [see Warnings and Precautions (5.2)] | Hematologic adverse reaction requiring transfusion | - Consider platelet transfusion for patients with platelet count ≤10,000/mcL. If there are other risk factors such as coadministration of anticoagulation or antiplatelet drugs, consider interrupting these drugs and/or transfusion at a higher platelet count. - Resume at the reduced dose of AKEEGA 100 mg/1,000 mg once daily.
Hepatotoxicity [see Warnings and Precautions (5.4)] | ALT and/or AST greater than 5 × ULN or total bilirubin greater than 3 × ULN | - Withhold AKEEGA and closely monitor liver function. - Permanently discontinue AKEEGA if: ALT or AST ≥ 20 times the ULN – OR– ALT > 3 × ULN and total bilirubin > 2 × ULN in the absence of biliary obstruction or other causes responsible for the concurrent elevation -OR- Hepatotoxicity recurs at the reduced dose 100 mg/500 mg. - When AST and ALT resolves to less ≤ 2.5 × ULN and total bilirubin ≤ 1.5 × ULN, AKEEGA may be resumed at the reduced dose of 100 mg/500 mg once daily. When resumed, monitor serum transaminases every two weeks for three months, monthly thereafter, and as clinically indicated.
Other non-hematological adverse reactions that persist despite medical management [see Warnings and Precautions (5)and Adverse Reactions (6.1)] | Grade 3 or 4 [Discontinue AKEEGA in patients who develop hypertensive crisis or other severe cardiovascular adverse reactions [see Warnings and Precautions (5.3)].] | - Withhold AKEEGA until resolution of adverse reaction or for a maximum of 28 days. - If resolves in 28 days or less, AKEEGA may be resumed at the reduced dose. - Permanently discontinue AKEEGA if adverse reaction(s) has not resolved after 28 days or Grade 3 or 4 adverse reaction reoccurs after dose reduction.

3 DOSAGE FORMS AND STRENGTHS

Tablets

- 50 mg niraparib/500 mg abiraterone acetate: yellowish orange to yellowish brown, oval, film-coated tablets debossed with "N 50 A" on one side and plain on the other side.
- 100 mg niraparib/500 mg abiraterone acetate: orange, oval, film-coated tablets debossed with "N 100 A" on one side and plain on the other side.

4 CONTRAINDICATIONS

None.

5 WARNINGS AND PRECAUTIONS

5.1 Myelodysplastic Syndrome/Acute Myeloid Leukemia

AKEEGA may cause myelodysplastic syndrome/acute myeloid leukemia (MDS/AML).

In the individual AMPLITUDE and MAGNITUDE studies, MDS or AML, including cases with fatal outcomes, were reported in 0.6% (2/347) and 0.5% (1/212) of patients treated with AKEEGA plus prednisone, respectively.

All patients in other tumor types treated with niraparib, a component of AKEEGA, who developed secondary MDS/cancer-therapy-related AML had received previous chemotherapy with platinum agents and/or other DNA-damaging agents, including radiotherapy.

For suspected MDS/AML or prolonged hematological toxicities, refer the patient to a hematologist for further evaluation. Discontinue AKEEGA if MDS/AML is confirmed.

5.2 Myelosuppression

AKEEGA may cause myelosuppression (anemia, thrombocytopenia, or neutropenia).

In AMPLITUDE, Grade 3–4 anemia, neutropenia, and thrombocytopenia were reported, respectively in 29%, 10%, and 4.9% of patients receiving AKEEGA. Overall, 25% of patients with anemia required a red blood cell transfusion, including 15% who required more than one transfusion. Discontinuation due to anemia occurred in 1.2% of patients.

In MAGNITUDE Cohort 1, Grade 3–4 anemia, thrombocytopenia, and neutropenia were reported, respectively in 28%, 8%, and 7% of patients receiving AKEEGA. Overall, 27% of patients with anemia required a red blood cell transfusion, including 19.5% who required more than one transfusion. Discontinuation due to anemia occurred in 3% of patients.

Monitor complete blood counts weekly during the first month of AKEEGA treatment, every two weeks for the next two months, monthly for the remainder of the first year and then every other month, and as clinically indicated. Do not start AKEEGA until patients have adequately recovered from hematologic toxicity caused by previous therapy. If hematologic toxicities do not resolve within 28 days following interruption, discontinue AKEEGA and refer the patient to a hematologist for further investigations, including bone marrow analysis and blood sample for cytogenetics [see Dosage and Administration (2.3)] .

5.3 Hypokalemia, Fluid Retention, and Cardiovascular Adverse Reactions

AKEEGA may cause hypokalemia and fluid retention as a consequence of increased mineralocorticoid levels resulting from CYP17 inhibition [see Clinical Pharmacology (12.1)] . In post-marketing experience, QT prolongation and Torsades de Pointes have been observed in patients who develop hypokalemia while taking abiraterone acetate, a component of AKEEGA. Hypertension and hypertensive crisis have also been reported in patients treated with niraparib, a component of AKEEGA.

In AMPLITUDE, which used prednisone 5 mg daily in combination with AKEEGA, Grades 3–4 hypokalemia was detected in 9% of patients on the AKEEGA arm, and Grades 3–4 hypertension was observed in 30% of patients on the AKEEGA arm.

In MAGNITUDE Cohort 1, which used prednisone 10 mg daily in combination with AKEEGA, Grade 3–4 hypokalemia was detected in 2.7% of patients on the AKEEGA arm and Grade 3–4 hypertension was observed in 14% of patients on the AKEEGA arm.

Monitor patients for hypertension, hypokalemia, and fluid retention at least weekly for the first two months, then once a month. Closely monitor patients whose underlying medical conditions might be compromised by increases in blood pressure, hypokalemia, or fluid retention, such as those with heart failure, recent myocardial infarction, cardiovascular disease, or ventricular arrhythmia. Control hypertension and correct hypokalemia before and during treatment with AKEEGA. Discontinue AKEEGA in patients who develop hypertensive crisis or other severe cardiovascular adverse reactions.

The safety of AKEEGA in patients with New York Heart Association (NYHA) Class II to IV heart failure has not been established because these patients were excluded from AMPLITUDE and MAGNITUDE.

5.4 Hepatotoxicity

AKEEGA may cause hepatotoxicity.

Hepatotoxicity in patients receiving abiraterone acetate, a component of AKEEGA, has been reported in clinical trials. In post-marketing experience, there have been abiraterone acetate-associated severe hepatic toxicity, including fulminant hepatitis, acute liver failure, and deaths.

In AMPLITUDE, Grade 3–4 ALT or AST increases (at least 5 × ULN) were reported in 1.9% and 1.3% of patients, respectively.

In MAGNITUDE Cohort 1, Grade 3–4 ALT or AST increases (at least 5 × ULN) were reported in 1.8% and 0.9% of patients, respectively.

The safety of AKEEGA in patients with moderate or severe hepatic impairment has not been established as these patients were excluded from AMPLITUDE and MAGNITUDE.

Measure serum transaminases (ALT and AST) and bilirubin levels prior to starting treatment with AKEEGA, every two weeks for the first three months of treatment and monthly thereafter. Promptly measure serum total bilirubin, AST, and ALT if clinical symptoms or signs suggestive of hepatotoxicity develop. Elevations of AST, ALT, or bilirubin from the patient's baseline should prompt more frequent monitoring and may require dosage modifications [see Dosage and Administration (2.3)].

Permanently discontinue AKEEGA for patients who develop a concurrent elevation of ALT greater than 3 × ULN and total bilirubin greater than 2 × ULN in the absence of biliary obstruction or other causes responsible for the concurrent elevation, or in patients who develop ALT or AST ≥20 × ULN at any time after receiving AKEEGA.

5.5 Adrenocortical Insufficiency

AKEEGA may cause adrenal insufficiency.

Adrenocortical insufficiency has been reported in clinical trials in patients receiving abiraterone acetate, a component of AKEEGA, in combination with prednisone, following interruption of daily steroids and/or with concurrent infection or stress. Monitor patients for symptoms and signs of adrenocortical insufficiency, particularly if patients are withdrawn from prednisone, have prednisone dose reductions, or experience unusual stress. Symptoms and signs of adrenocortical insufficiency may be masked by adverse reactions associated with mineralocorticoid excess seen in patients treated with abiraterone acetate. If clinically indicated, perform appropriate tests to confirm the diagnosis of adrenocortical insufficiency. Increased doses of corticosteroids may be indicated before, during, and after stressful situations.

5.6 Hypoglycemia

AKEEGA may cause hypoglycemia in patients being treated with other medications for diabetes.

Severe hypoglycemia has been reported when abiraterone acetate, a component of AKEEGA, was administered to patients receiving medications containing thiazolidinediones (including pioglitazone) or repaglinide [see Drug Interactions (7.2)] .

Monitor blood glucose in patients with diabetes during and after discontinuation of treatment with AKEEGA. Assess if antidiabetic drug dosage needs to be adjusted to minimize the risk of hypoglycemia.

5.7 Increased Fractures and Mortality in Combination with Radium 223 Dichloride

AKEEGA with prednisone is not recommended for use in combination with Ra-223 dichloride outside of clinical trials.

The clinical efficacy and safety of concurrent initiation of abiraterone acetate plus prednisone/prednisolone and radium Ra 223 dichloride was assessed in a randomized, placebo-controlled multicenter study (ERA-223 trial) in 806 patients with asymptomatic or mildly symptomatic castration-resistant prostate cancer with bone metastases. The study was unblinded early based on an Independent Data Monitoring Committee recommendation.

At the primary analysis, increased incidences of fractures (29% vs 11%) and deaths (39% vs 36%) have been observed in patients who received abiraterone acetate plus prednisone/prednisolone in combination with radium Ra 223 dichloride compared to patients who received placebo in combination with abiraterone acetate plus prednisone.

It is recommended that subsequent treatment with Ra-223 not be initiated for at least five days after the last administration of AKEEGA, in combination with prednisone.

5.8 Posterior Reversible Encephalopathy Syndrome

AKEEGA may cause Posterior Reversible Encephalopathy Syndrome (PRES).

PRES has been observed in patients treated with niraparib as a single agent at higher than the recommended dose of niraparib included in AKEEGA.

Monitor all patients treated with AKEEGA for signs and symptoms of PRES. If PRES is suspected, promptly discontinue AKEEGA and administer appropriate treatment. The safety of reinitiating AKEEGA in patients previously experiencing PRES is not known.

5.9 Embryo-Fetal Toxicity

The safety and efficacy of AKEEGA have not been established in females. Based on animal reproductive studies and mechanism of action, AKEEGA can cause fetal harm and loss of pregnancy when administered to a pregnant female [see Clinical Pharmacology (12.1)] .

Niraparib has the potential to cause teratogenicity and/or embryo-fetal death since niraparib is genotoxic and targets actively dividing cells in animals and patients (e.g., bone marrow) [see Warnings and Precautions (5.2)and Nonclinical Toxicology (13.1)] .

In animal reproduction studies, oral administration of abiraterone acetate to pregnant rats during organogenesis caused adverse developmental effects at maternal exposures approximately ≥ 0.03 times the human exposure (AUC) at the recommended dose.

Advise males with female partners of reproductive potential to use effective contraception during treatment and for 4 months after the last dose of AKEEGA [see Use in Specific Populations (8.1, 8.3)] . Females who are or may become pregnant should handle AKEEGA with protection, e.g., gloves [see How Supplied/Storage and Handling (16)].

6 ADVERSE REACTIONS

The following adverse reactions are discussed elsewhere in the labeling:

- Myelodysplastic syndrome/acute myeloid leukemia [see Warnings and Precautions (5.1)]
- Myelosuppression [see Warnings and Precautions (5.2)]
- Hypokalemia, fluid retention, and cardiovascular adverse reactions [see Warnings and Precautions (5.3)]
- Hepatotoxicity [see Warnings and Precautions (5.4)]
- Adrenocortical insufficiency [see Warnings and Precautions (5.5)]
- Hypoglycemia [see Warnings and Precautions (5.6)]
- Increased fractures and mortality in combination with Radium 223 Dichloride [see Warnings and Precautions (5.7)]
- Posterior reversible encephalopathy syndrome [see Warnings and Precautions (5.8)]

6.1 Clinical Trial Experience

Because clinical trials are conducted under widely varying conditions, adverse reaction rates observed in the clinical trials of a drug cannot be directly compared to rates in the clinical trials of another drug and may not reflect the rates observed in practice.

The safety population described in the WARNINGS and PRECAUTIONS reflect exposure to AKEEGA (niraparib 200 mg and abiraterone acetate 1,000 mg) in BRCA2m patients (N=162) in the AMPLITUDE study and in BRCAm patients in Cohort 1 (N=113) in the MAGNITUDE study unless otherwise specified.

BRCA2-mutated Metastatic Castration-Sensitive Prostate Cancer (mCSPC)

The safety of AKEEGA in patients with BRCA2m mCSPC was evaluated in AMPLITUDE [see Clinical Studies (14.1)]. Patients were randomized to receive either AKEEGA (niraparib 200 mg and abiraterone acetate 1,000 mg once daily) (n=162), or placebo and abiraterone acetate (n=161) until unacceptable toxicity or progression. Patients in both arms also received prednisone 5 mg daily. The median duration of exposure for AKEEGA was 26 months (range: 0 to 48 months).

Serious adverse reactions occurred in 36% of patients who received AKEEGA. Serious adverse reactions reported in >2% of patients included anemia (4.9%), and pneumonia (3.7%). Fatal adverse reactions occurred in 4.9% of patients who received AKEEGA, including sudden death (1.9%), COVID-19 pneumonia (1.2%), pneumocystis jirovecii pneumonia (0.6%), pneumonia (0.6%), and cardio-respiratory arrest (0.6%).

Permanent discontinuation of any component of AKEEGA due to an adverse reaction occurred in 13% of patients.

Dosage interruptions of any component of AKEEGA due to an adverse reaction occurred in 67% of patients. Adverse reactions which required dosage interruption in >2% of patients included anemia (30%), COVID-19 (10%), hypertension (9%), neutropenia (8%), thrombocytopenia (8%), hypokalemia (7%), vomiting (4.9%), fatigue (4.3%), diarrhea (2.5%), and pneumonia (2.5%).

Dose reductions of any component of AKEEGA due to an adverse reaction occurred in 25% of patients. Adverse reactions which required dose reductions in >2% of patients included anemia (17%).

The most common adverse reactions (>20%), including laboratory abnormalities, in patients who received AKEEGA were decreased hemoglobin, decreased lymphocyte count, hypertension, decreased neutrophil count, musculoskeletal pain, decreased platelet count, constipation, fatigue, decreased potassium, increase creatinine, nausea, increased alkaline phosphate, increased aspartate aminotransferase, respiratory tract infection, arrhythmia, increased blood bilirubin, and fluid retention/edema.

Table 2: Adverse Reactions (>20%) in Patients with BRCA2m mCSPC Who Received AKEEGA (with a Difference of ≥5% Compared to Placebo) in AMPLITUDE
Adverse Reaction | AKEEGA (N=162) |  | Placebo with Abiraterone Acetate (N=161)
Adverse Reaction | All Grades % | Grade 3 or 4 % | All Grades % | Grade 3 or 4 %
Vascular disorders
Hypertension [Grouped terms including multiple similar terms] | 51 | 31 | 36 | 19
Musculoskeletal and connective tissue disorders
Musculoskeletal pain | 45 | 6 | 58 | 4.3
Gastrointestinal disorders
Constipation | 41 | 0 | 17 | 0.6
Nausea | 30 | 0 | 17 | 0
General disorders and administration
Fatigue | 39 | 4.3 | 29 | 3.1
Respiratory, thoracic and mediastinal disorders
Respiratory Tract Infection | 23 | 0.6 | 13 | 0.6
Cardiac disorders
Arrhythmia | 23 | 3.7 | 9 | 2.5

Clinically relevant adverse reactions that occurred in ≤20% of patients receiving AKEEGA plus prednisone were hot flush (18%), vomiting (17%), dizziness (17%), abdominal pain (15%), weight decreased (14%), diarrhea (14%), decreased appetite (12%), headache (12%), hemorrhage (12%), dyspnea (10%), urinary tract infection (8%), pneumonia (7%), osteoporosis (4.9%), rash (3.7%), cardiac failure (3.1%), ischemic heart disease (4.9%), acute kidney injury (2.5%), pulmonary embolism (2.5%), and urosepsis (0.6%).

The most common select laboratory abnormalities (>20%) that worsened from baseline in patients who received AKEEGA are in Table 3.

Table 3: Select Laboratory Abnormalities (>20%) That Worsened from Baseline in Patients with BRCA2m mCSPC Who Received AKEEGA in AMPLITUDE
Laboratory Abnormality | AKEEGA [The denominator used to calculate the rate varied from 160 to 161 for placebo with abiraterone acetate plus prednisone and 159 to 162 for AKEEGA with prednisone based on the number of patients with a baseline value and at least one post-treatment value.] (N=162) |  | Placebo with Abiraterone Acetate (N=161)
Laboratory Abnormality | All Grades (%) | Grade 3 or 4 (%) | All Grades (%) | Grade 3 or 4 (%)
Hematology
Decreased Hemoglobin | 74 | 29 | 53 | 1.9
Decreased Lymphocyte Count | 59 | 20 | 37 | 13
Decreased Neutrophil Count | 49 | 10 | 19 | 3.1
Decreased Platelet Count | 41 | 4.9 | 23 | 0.6
Chemistry
Decreased Potassium | 38 | 9 | 29 | 10
Increased Creatinine | 30 | 1.3 | 16 | 2.5
Increased Alkaline Phosphatase | 28 | 0.6 | 24 | 3.1
Increased Aspartate Aminotransferase | 24 | 1.3 | 33 | 2.5
Increased Blood Bilirubin | 22 | 0 | 11 | 0

BRCA-mutated Metastatic Castration-Resistant Prostate Cancer

The safety of AKEEGA in patients with BRCAm mCRPC was evaluated in Cohort 1 of MAGNITUDE [see Clinical Studies (14.2)]. Patients were randomized to receive either AKEEGA (niraparib 200 mg and abiraterone acetate 1,000 mg once daily) (n=113), or placebo and abiraterone acetate (n=112) until unacceptable toxicity or progression. Patients in both arms also received prednisone 10 mg daily. The median duration of exposure for AKEEGA was 18 months (range: 0 to 37 months).

Serious adverse reactions occurred in 41% of patients who received AKEEGA. Serious adverse reactions reported in >2% of patients included COVID-19 (7%), anemia (4.4%), pneumonia (3.5%), and hemorrhage (3.5%). Fatal adverse reactions occurred in 9% of patients who received AKEEGA, including COVID-19 (5%), cardiopulmonary arrest (1%), dyspnea (1%), pneumonia (1%), and septic shock (1%).

Permanent discontinuation of any component of AKEEGA due to an adverse reaction occurred in 15% of patients. Adverse reactions which resulted in permanent discontinuation of AKEEGA in > 2% of patients included COVID-19 (4.4%), anemia (2.7%), asthenia (2.7%), and vomiting (2.7%).

Dosage interruptions of any component of AKEEGA due to an adverse reaction occurred in 50% of patients. Adverse reactions which required dosage interruption in > 2% of patients included anemia (23%), thrombocytopenia (12%), neutropenia (7%), COVID-19 (6%), fatigue (3.5%), asthenia (3.5%), nausea (3.5%), pneumonia (2.7%), hematuria (2.7%), and vomiting (2.7%).

Dose reductions of any component of AKEEGA due to an adverse reaction occurred in 28% of patients. Adverse reactions which required dose reductions in > 2% of patients included anemia (12%), thrombocytopenia (4.4%), and fatigue (2.7%).

The most common adverse reactions (>20%), including laboratory abnormalities, in patients who received AKEEGA were hemoglobin decreased, lymphocyte decreased, musculoskeletal pain, fatigue, platelets decreased, constipation, alkaline phosphatase increased, hypertension, nausea, neutrophils decreased, creatinine increased, potassium increased, potassium decreased, and aspartate aminotransferase increased.

Tables 4 and 5 summarize adverse reactions and laboratory abnormalities for patients with BRCAm mCRPC in MAGNITUDE, respectively.

Table 4: Adverse Reactions (>10%) in Patients with BRCAm mCRPC Who Received AKEEGA in MAGNITUDE
 | AKEEGA (N=113) |  | Placebo with Abiraterone Acetate (N=112)
Adverse Reaction | All Grades % | Grade 3 or 4 % | All Grades % | Grade 3 or 4 %
Musculoskeletal and connective tissue disorders
Musculoskeletal pain [Grouped terms including multiple similar terms.] | 44 | 4 | 42 | 5
General disorders and administration site conditions
Fatigue | 43 | 5 | 30 | 4
Edema | 17 | 0 | 9 | 0
Pyrexia | 10 | 2 | 6 | 0
Gastrointestinal disorders
Constipation | 34 | 1 | 20 | 0
Vomiting | 15 | 0 | 7 | 1
Nausea | 33 | 1 | 21 | 0
Abdominal pain | 12 | 2 | 12 | 1
Vascular disorders
Hypertension | 33 | 14 | 27 | 17
Hemorrhage | 12 | 2 | 8 | 1
Respiratory, thoracic and mediastinal disorders
Dyspnea | 15 | 1 | 8 | 3
Cough | 12 | 0 | 6 | 0
Metabolism and nutrition disorders
Decreased appetite | 15 | 2 | 8 | 0
Nervous system disorders
Dizziness | 14 | 0 | 10 | 0
Headache | 12 | 1 | 9 | 0
Infections and infestations
COVID-19 | 13 | 7 | 9 | 4
Urinary tract infection | 12 | 3 | 9 | 1
Psychiatric disorders
Insomnia | 12 | 0 | 4 | 0
Investigations
Weight decreased | 10 | 1 | 4 | 1
Cardiac disorders
Arrhythmia | 10 | 2 | 4 | 1
Injury, poisoning and procedural complications
Fall | 10 | 1 | 13 | 4

Clinically relevant adverse events that occurred in <10% of patients receiving AKEEGA plus prednisone were rash (7%), alanine aminotransferase increased (5%), aspartate aminotransferase increased (5%), cerebrovascular accident (4.4%), pulmonary embolism (2.7%), deep vein thrombosis (2.7%), and acute kidney injury (2.7%).

Table 5: Select Laboratory Abnormalities (>20%) That Worsened from Baseline in Patients with BRCAm mCRPC Who Received AKEEGA in MAGNITUDE
 | AKEEGA [The denominator used to calculate the rate varied from 111 to 112 for placebo with abiraterone acetate plus prednisone and 113 for AKEEGA with prednisone based on the number of patients with a baseline value and at least one post-treatment value.] (N=113) |  | Placebo with Abiraterone Acetate (N=112)
Laboratory Abnormality | All Grades (%) | Grade 3 or 4 (%) | All Grades (%) | Grade 3 or 4 (%)
Hematology
Hemoglobin decreased | 67 | 26 | 53 | 7
Lymphocyte decreased | 55 | 22 | 32 | 13
Platelets decreased | 37 | 8 | 22 | 1.8
Neutrophils decreased | 32 | 7 | 16 | 2.7
Chemistry
Alkaline Phosphatase increased | 34 | 1.8 | 29 | 1.8
Creatinine increased | 30 | 0 | 13 | 1.8
Potassium increased | 25 | 0.9 | 21 | 3.6
Potassium decreased | 20 | 5 | 20 | 5
Aspartate Aminotransferase increased | 20 | 1.8 | 25 | 2.7

Other Clinical Trial Experience

The following adverse reactions have been reported with the individual components of AKEEGA but were not observed in AMPLITUDE or MAGNITUDE Cohort 1: myopathy, rhabdomyolysis, adrenal insufficiency, allergic alveolitis, febrile neutropenia, anaphylactic reaction, posterior reversible encephalopathy (PRES), and hypertensive crisis.

7 DRUG INTERACTIONS

7.1 Effect of Other Drugs on AKEEGA

Effect of CYP3A4 Inducers

Avoid coadministration with strong CYP3A4 inducers [see Clinical Pharmacology (12.3)] .

Abiraterone is a substrate of CYP3A4. Strong CYP3A4 inducers may decrease abiraterone concentrations [see Clinical Pharmacology (12.3)], which may reduce the effectiveness of abiraterone.

7.2 Effects of AKEEGA on Other Drugs

CYP2D6 Substrates

Avoid coadministration unless otherwise recommended in the Prescribing Information for CYP2D6 substrates for which minimal changes in concentration may lead to serious toxicities. If alternative treatments cannot be used, consider a dose reduction of the concomitant CYP2D6 substrate drug.

Abiraterone is a CYP2D6 moderate inhibitor. AKEEGA increases the concentration of CYP2D6 substrates [see Clinical Pharmacology (12.3)], which may increase the risk of adverse reactions related to these substrates.

CYP2C8 Substrates

Monitor patients for signs of toxicity related to a CYP2C8 substrate for which a minimal change in plasma concentration may lead to serious or life-threatening adverse reactions.

Abiraterone is a CYP2C8 inhibitor. AKEEGA increases the concentration of CYP2C8 substrates [see Clinical Pharmacology (12.3)], which may increase the risk of adverse reactions related to these substrates.

8 USE IN SPECIFIC POPULATIONS

8.1 Pregnancy

Risk Summary

The safety and efficacy of AKEEGA have not been established in females. Based on findings from animal studies and mechanism of action [see Clinical Pharmacology (12.1)] , AKEEGA can cause fetal harm and potential loss of pregnancy.

There are no human data on the use of AKEEGA in pregnant women.

Niraparib has the potential to cause teratogenicity and/or embryo-fetal death since niraparib is genotoxic and targets actively dividing cells in animals and patients (e.g., bone marrow) [see Warnings and Precautions (5.2)and Nonclinical Toxicology (13.1)] . Due to the potential risk to a fetus based on its mechanism of action, animal developmental and reproductive toxicology studies were not conducted with niraparib.

In animal reproduction studies, oral administration of abiraterone acetate to pregnant rats during organogenesis caused adverse developmental effects at maternal exposures approximately ≥ 0.03 times the human exposure (AUC) at the recommended dose (see Data) .

Data

Animal Data

Niraparib

Niraparib is genotoxic and targets actively dividing cells. Animal developmental and reproductive toxicology studies were not conducted with niraparib.

Abiraterone Acetate

In an embryo-fetal developmental toxicity study in rats, abiraterone acetate caused developmental toxicity when administered at oral doses of 10, 30 or 100 mg/kg/day throughout the period of organogenesis (gestational days 6–17). Findings included embryo-fetal lethality (increased post implantation loss and resorptions and decreased number of live fetuses), fetal developmental delay (skeletal effects) and urogenital effects (bilateral ureter dilation) at doses ≥10 mg/kg/day, decreased fetal ano-genital distance at ≥30 mg/kg/day, and decreased fetal body weight at 100 mg/kg/day. Doses ≥10 mg/kg/day caused maternal toxicity. The doses tested in rats resulted in systemic exposures (AUC) approximately 0.03, 0.1 and 0.3 times, respectively, the AUC in patients receiving 1,000 mg daily of abiraterone acetate.

8.2 Lactation

Risk Summary

The safety and efficacy of AKEEGA have not been established in females. There is no information available on the presence of niraparib or abiraterone in human milk, or on the effects on the breastfed child or milk production.

8.3 Females and Males of Reproductive Potential

Contraception

Males

Based on findings in animal reproduction studies and its mechanism of action, advise males with female partners of reproductive potential to use effective contraception during treatment and for 4 months after the last dose of AKEEGA [see Use in Specific Populations (8.1)] .

Infertility

Based on animal studies, AKEEGA may impair fertility in males of reproductive potential [see Nonclinical Toxicology (13.1)] .

8.4 Pediatric Use

Safety and effectiveness of AKEEGA in pediatric patients have not been established.

8.5 Geriatric Use

Of the 162 patients with BRCA2gene alteration(s) who received AKEEGA in AMPLITUDE, 40% of patients were less than 65 years, 36% of patients were 65 years to 74 years, and 23% were 75 years and over.

Of the 113 patients with BRCAgene alteration(s) who received AKEEGA in MAGNITUDE, 34.5% of patients were less than 65 years, 38.9% of patients were 65 years to 74 years, and 26.5% were 75 years and over.

No overall differences in effectiveness were observed between patients 65 years of age or older and younger patients in AMPLITUDE or MAGNITUDE. Patients 75 years of age or older who received AKEEGA experienced a higher incidence of fatal adverse reactions than younger patients. The incidence of fatal adverse reactions was 4.3% in patients younger than 75 and 13% in patients 75 or older.

8.6 Hepatic Impairment

Avoid use of AKEEGA in patients with moderate or severe hepatic impairment [see Warnings and Precautions (5.4)and Clinical Pharmacology (12.3)] .

No dosage modification is necessary for patients with mild hepatic impairment.

8.7 Renal Impairment

Monitor patients with severe renal impairment for increased adverse reactions and modify dosage as recommended for adverse reactions [see Clinical Pharmacology (12.3)].

No dosage modification is recommended for patients with mild to moderate renal impairment.

10 OVERDOSAGE

In the event of an overdose, administration of AKEEGA should be stopped and general supportive measures undertaken, including monitoring for arrhythmias and cardiac failure and assessing liver function.

There is no specific treatment in the event of AKEEGA overdose.

11 DESCRIPTION

AKEEGA® (niraparib and abiraterone acetate) tablets contain niraparib tosylate (as the monohydrate) and abiraterone acetate.

Niraparib

Niraparib is a poly (ADP-ribose) polymerase (PARP) inhibitor. The chemical name for niraparib tosylate monohydrate is 2-{4-[(3S)-piperidin-3-yl]phenyl}- 2H-indazole 7-carboxamide 4-methylbenzenesulfonate hydrate (1:1:1). The molecular formula is C26 H30 N4 O5 S and it has a molecular weight of 510.61 g/mol. The molecular structure is shown below:

Niraparib tosylate monohydrate is a white to off-white, non-hygroscopic crystalline solid. Niraparib tosylate monohydrate is highly soluble in aqueous media over the pH range 1.2 to 6.8 (1.65–1.77 mg/mL determined at 37 ± 1°C).

Abiraterone Acetate

Abiraterone acetate is the acetyl ester of abiraterone. Abiraterone is an inhibitor of CYP17 (17α-hydroxylase/C17,20-lyase). Its molecular formula is C26 H33 N O2 and it has a molecular weight of 391.55 g/mol. Abiraterone acetate is designated chemically as (3β)-17-(3-pyridinyl) androsta-5,16-dien-3-yl acetate and its structure is:

Abiraterone acetate is a white to off-white, non-hygroscopic, crystalline powder. Abiraterone acetate is a lipophilic compound with an octanol-water partition coefficient of 5.12 (Log P) and is practically insoluble in water. The pKa of the aromatic nitrogen is 5.19.

AKEEGA tablets are supplied as 50 mg/500 mg niraparib/abiraterone acetate and 100 mg/500 mg niraparib/abiraterone acetate film-coated tablets for oral administration.

Each AKEEGA tablet (50 mg/500 mg) contains 50 mg of niraparib (equivalent to 76.9 mg niraparib tosylate) and 500 mg of abiraterone acetate.

Each AKEEGA tablet (100 mg/500 mg) contains 100 mg of niraparib (equivalent to 153.7 mg niraparib tosylate) and 500 mg of abiraterone acetate.

AKEEGA tablet core contains the following inactive ingredients: colloidal anhydrous silica, crospovidone, hypromellose, lactose monohydrate, magnesium stearate, silicified microcrystalline cellulose, sodium lauryl sulfate.

- The 50 mg/500 mg tablets are finished with film-coating comprising the following inactive ingredients: iron oxide black, iron oxide red, iron oxide yellow, sodium lauryl sulphate, glycerol monocaprylocaprate, polyvinyl alcohol, talc, and titanium dioxide.
- The 100 mg/500 mg tablets are finished with film-coating comprising the following inactive ingredients: iron oxide red, iron oxide yellow, sodium lauryl sulphate, glycerol monocaprylocaprate, polyvinyl alcohol, talc, and titanium dioxide.

12 CLINICAL PHARMACOLOGY

12.1 Mechanism of Action

Niraparib is an inhibitor of PARP enzymes, including PARP-1 and PARP-2, that play a role in DNA repair. In vitro studies have shown that niraparib-induced cytotoxicity may involve inhibition of PARP enzymatic activity and increased formation of PARP-DNA complexes resulting in DNA damage, apoptosis, and cell death. Increased niraparib‑induced cytotoxicity was observed in tumor cell lines with or without deficiencies in BRCA1/2. Niraparib decreased tumor growth in mouse xenograft models of human cancer cell lines with deficiencies in BRCA1/2 and in human patient‑derived xenograft tumor models with homologous recombination deficiency (HRD) that had either mutated or wild-type BRCA1/2.

Abiraterone acetate is converted in vivo to abiraterone, an androgen biosynthesis inhibitor, that inhibits 17 α-hydroxylase/C17,20-lyase (CYP17). This enzyme is expressed in testicular, adrenal, and prostatic tumor tissues and is required for androgen biosynthesis.

CYP17 catalyzes two sequential reactions: 1) the conversion of pregnenolone and progesterone to their 17α-hydroxy derivatives by 17α-hydroxylase activity and 2) the subsequent formation of dehydroepiandrosterone (DHEA) and androstenedione, respectively, by C17, 20 lyase activity. DHEA and androstenedione are androgens and are precursors of testosterone. Inhibition of CYP17 by abiraterone can also result in increased mineralocorticoid production by the adrenals [see Warnings and Precautions (5.9)] .

Androgen sensitive prostatic carcinoma responds to treatment that decreases androgen levels. Androgen deprivation therapies, such as treatment with GnRH agonists or orchiectomy, decrease androgen production in the testes but do not affect androgen production by the adrenals or in the tumor.

Abiraterone decreased serum testosterone and other androgens in patients in the placebo-controlled clinical trial. It is not necessary to monitor the effect of abiraterone on serum testosterone levels.

Changes in serum prostate specific antigen (PSA) levels may be observed but have not been shown to correlate with clinical benefit in individual patients.

In mouse xenograft models of prostate cancer, the combination of niraparib and abiraterone acetate increased anti-tumor activity when compared to either drug alone.

12.2 Pharmacodynamics

The exposure-response relationship and time-course of pharmacodynamic response for the safety and effectiveness of AKEEGA have not been fully characterized.

Hypertension and Cardiovascular Effects

Niraparib has the potential to cause effects on pulse rate and blood pressure in patients, which may be related to pharmacological inhibition of the dopamine transporter (DAT), norepinephrine transporter (NET), and serotonin transporter (SERT) [see Nonclinical Toxicology (13.2)] .

Niraparib increased mean pulse rate by 22.4 to 24.1 beats/min, mean systolic blood pressure by 24.5 mmHg, and mean diastolic pressure by 16.5 mmHg relative to 14.0 to 15.8 beats per min, 18.3 to 19.6 mmHg, and 11.6 mmHg in the placebo arm.

Cardiac Electrophysiology

No large (>20 ms) increases in the mean QTc interval were detected following the treatment of niraparib 300 mg once daily or 1,000 mg of abiraterone acetate once daily.

12.3 Pharmacokinetics

Niraparib

Following the administration of AKEEGA, the mean (coefficient of variation [CV%]) Cmax, ss was 831 ng/mL (32%) and AUC0–24h, ss was 13,616 ng∙h/mL (36%). The accumulation ratio following daily administration of AKEEGA was 3.5-, and 2.6-fold for niraparib AUC0–24h and Cmax.

Niraparib exhibits dose proportional increase in Cmax and AUC in the dose range of 30 mg (0.15 times the recommended dosage) to 400 mg (2 times the recommended dosage).

Abiraterone Acetate

Following the administration of AKEEGA, the mean (CV%) Cmax,ss was 151 ng/mL (59%) and AUC0–24h,ss was 707 ng∙h/mL (59%) for abiraterone. The accumulation ratio following daily administration of AKEEGA was 2-, and 1.8-fold for abiraterone AUC0–24h and Cmax.

No major deviation from dose proportionality was observed for abiraterone acetate in the dose range of 250 mg (0.25 times the recommended dosage) to 1,000 mg (the recommended dosage).

Absorption

Niraparib

The median Tmax was 3 hours after dosing. The absolute bioavailability of niraparib is approximately 73%.

Abiraterone Acetate

The median Tmax of abiraterone was 1.5 hours after dosing.

Administration of abiraterone acetate with food, compared with administration in a fasted state, results in up to a 10-fold (AUC) and up to a 17-fold (Cmax) increase in mean systemic exposure of abiraterone, depending on the fat content of the meal. Given the normal variation in the content and composition of meals, taking abiraterone acetate with meals has the potential to result in increased and highly variable exposures.

Distribution

Niraparib

The apparent volume of distribution of niraparib was 1,117 L. Niraparib is 83% bound to human plasma proteins.

Abiraterone Acetate

The apparent volume of distribution of abiraterone was 25,774 L. Abiraterone is highly bound (>99%) to the human plasma proteins, albumin and alpha-1 acid glycoprotein.

Elimination

Niraparib

The mean t½ of niraparib when given in combination was approximately 62 hours (CV%: 42%) and apparent CL/F was 16.7 L/h (CV%: 27%).

Abiraterone Acetate

The mean t½ of abiraterone when given in combination was approximately 20 hours (CV%: 7.8%) and apparent CL/F was 1673 L/h (CV%: 24%).

Metabolism

Niraparib

Niraparib is metabolized by carboxylesterases.

Abiraterone Acetate

Abiraterone acetate is rapidly converted in vivo to abiraterone. CYP3A4 and SULT2A1 are the enzymes involved in the metabolism of abiraterone.

Excretion

Niraparib

About 48% (33% to 60%) of the radiolabeled dose was recovered in urine and 39% (28% to 47%) in feces. Unchanged niraparib accounted for 11% and 19% of the administered dose recovered in urine and feces, respectively.

Abiraterone Acetate

Approximately 88% of the radiolabeled dose is recovered in feces and 5% in urine. Unchanged abiraterone acetate and abiraterone accounted for 55% and 22% of the administered dose recovered in the feces, respectively.

Specific Populations

No clinically significant effects on the PK of niraparib and abiraterone were observed based on body weight (43.3–165 kg for niraparib and 46–165 kg for abiraterone), age (45–90 years for niraparib and 43–90 years for abiraterone), race/ethnicity (White, Asian, and Hispanic) and mild to moderate renal impairment (CLcr: 30–90 mL/min). Severe renal impairment (CLcr: 15–30 mL/min) has not been studied.

Hepatic Impairment

Niraparib

Mild hepatic impairment did not affect the exposure of niraparib. Moderate hepatic impairment (Total bilirubin > 1.5 to 3 × ULN and any aspartate aminotransferase value) increased niraparib AUC by 56% compared to that of patients with normal hepatic function.

Abiraterone Acetate

Mild (Child-Pugh score of 5 to 6; Child-Turcotte-Pugh Class A) hepatic impairment increased abiraterone (AUC) by 1.1-fold and moderate (Child-Pugh score of 7 to 9; Child-Turcotte-Pugh Class B) hepatic impairment increased abiraterone (AUC) by 3.6-fold compared to subjects with normal hepatic function.

Severe (Child-Pugh score of 10 to 15; Child-Turcotte-Pugh Class C) hepatic impairment increased abiraterone AUC by 7-fold and the fraction of free drug increased by 2-fold in subjects compared to subjects with normal hepatic function.

Drug Interactions Studies

Niraparib

In Vitro Studies

- Inhibition of Cytochrome P450 (CYP) Enzymes: Niraparib is not an inhibitor of CYP1A2, CYP2B6, CYP2C8, CYP2C9, CYP2C19, CYP2D6, and CYP3A4.
- Induction of CYP Enzymes:Niraparib is not a CYP3A4 inducer. Niraparib induces CYP1A2 in vitro.
- Inhibition of Uridine 5'-Diphospho-Glucuronosyltransferases (UGTs): Niraparib did not inhibit UGT1A1, UGT1A4, UGT1A9, and UGT2B7.
- Inhibition of Transporter Systems: Niraparib inhibits BCRP, but does not inhibit P-gp, BSEP, or MRP2.
  Niraparib inhibits MATE 1 and 2.
- Substrate of Transporter Systems: Niraparib is a substrate of P-gp and BCRP. Niraparib is not a substrate of BSEP, MRP2, or MATE1 or 2.

Abiraterone Acetate

Clinical Studies

- Effect of Strong CYP3A4 Inducers on Abiraterone: Coadministration of rifampin (strong CYP3A4 inhibitor) decreased abiraterone mean AUC by 55%.
- Effect of Strong CYP3A4 Inhibitors on Abiraterone: Coadministration of ketoconazole (strong CYP3A4 inhibitor) had no clinically meaningful effect on the pharmacokinetics of abiraterone.
- Effect of Abiraterone Acetate on CYP2D6 Substrates: The Cmax and AUC of dextromethorphan (CYP2D6 substrate) were increased 2.8- and 2.9-fold, respectively when dextromethorphan 30 mg was given with abiraterone acetate 1,000 mg daily (plus prednisone). The AUC for dextrorphan, the active metabolite of dextromethorphan, increased approximately 1.3-fold.
- Effect of Abiraterone Acetate on CYP1A2 Substrates: When abiraterone acetate (plus prednisone) was given with a single dose of 100 mg theophylline (CYP1A2 substrate), no increase in systemic exposure of theophylline was observed.
- Effect of Abiraterone Acetate on CYP2C8 Substrates: The AUC of pioglitazone (CYP2C8 substrate) was increased by 46% when pioglitazone was given to healthy subjects with a single dose of abiraterone acetate.

In vitro Studies

- Cytochrome P450 (CYP) Enzymes: Abiraterone is a substrate of CYP3A4 and has the potential to inhibit CYP1A2, CYP2D6, CYP2C8 and to a lesser extent CYP2C9, CYP2C19 and CYP3A4/5.
- Transporter Systems: Abiraterone acetate and abiraterone are not substrates of P-gp. Abiraterone acetate is an inhibitor of P-gp. Abiraterone and its major metabolites were inhibitors of OATP1B1.

13 NONCLINICAL TOXICOLOGY

13.1 Carcinogenesis, Mutagenesis, Impairment of Fertility

Niraparib

Carcinogenicity studies have not been conducted with niraparib.

Niraparib was clastogenic in an in vitro mammalian chromosomal aberration assay and in an in vivo rat bone marrow micronucleus assay. This clastogenicity is consistent with genomic instability resulting from the primary pharmacology of niraparib and indicates potential for genotoxicity in humans. Niraparib was not mutagenic in a bacterial reverse mutation assay (Ames) test.

Fertility studies in animals have not been conducted with niraparib. In repeat-dose oral toxicity studies, niraparib was administered daily for up to 3 months' duration in rats and dogs. Reduced sperm, spermatids, and germ cells in epididymides and testes were observed at doses ≥10 mg/kg and ≥1.5 mg/kg in rats and dogs, respectively. These dose levels resulted in systemic exposures approximately 0.5 and 0.02 times, respectively, the human exposure (AUC0–24h) at the dose of 200 mg daily. There was a trend toward reversibility of these findings 4 weeks after dosing was stopped.

Abiraterone Acetate

A two-year carcinogenicity study was conducted in rats at oral abiraterone acetate doses of 5, 15, and 50 mg/kg/day for males and 15, 50, and 150 mg/kg/day for females. Abiraterone acetate increased the combined incidence of interstitial cell adenomas and carcinomas in the testes at all dose levels tested. This finding is considered to be related to the pharmacological activity of abiraterone. Rats are regarded as more sensitive than humans to developing interstitial cell tumors in the testes. Abiraterone acetate was not carcinogenic in female rats at exposure levels up to 0.8 times the human clinical exposure (1,000 mg daily) based on AUC. Abiraterone acetate was not carcinogenic in a 6-month study in the transgenic (Tg.rasH2) mouse.

Abiraterone acetate and abiraterone were not mutagenic in an in vitro microbial mutagenesis (Ames) assay or clastogenic in an in vitro cytogenetic assay using primary human lymphocytes or an in vivo rat micronucleus assay.

In repeat-dose toxicity studies in male rats (13- and 26-weeks) and monkeys (39-weeks), atrophy, aspermia/hypospermia, and hyperplasia in the reproductive system were observed at ≥50 mg/kg/day in rats and ≥250 mg/kg/day in monkeys and were consistent with the antiandrogenic pharmacological activity of abiraterone. These effects were observed in rats at systemic exposures similar to humans and in monkeys at exposures approximately 0.6 times the AUC in humans at 1,000 mg daily.

In a fertility study in male rats, reduced organ weights of the reproductive system, sperm counts, sperm motility, altered sperm morphology and decreased fertility were observed in animals dosed for 4 weeks at ≥30 mg/kg/day orally. Mating of untreated females with males that received 30 mg/kg/day oral abiraterone acetate resulted in a reduced number of corpora lutea, implantations and live embryos and an increased incidence of pre-implantation loss. Effects on male rats were reversible after 16 weeks from the last abiraterone acetate administration.

In a fertility study in female rats, animals dosed orally for 2 weeks until day 7 of pregnancy at ≥30 mg/kg/day had an increased incidence of irregular or extended estrous cycles and pre-implantation loss (300 mg/kg/day). There were no differences in mating, fertility, and litter parameters in female rats that received abiraterone acetate. Effects on female rats were reversible after 4 weeks from the last abiraterone acetate administration.

The dose of 30 mg/kg/day in rats is approximately 0.3 times the recommended dose of 1,000 mg/day based on body surface area.

In 13- and 26-week studies in rats and 13- and 39-week studies in monkeys, a reduction in circulating testosterone levels occurred with abiraterone acetate at approximately one half the human clinical exposure based on AUC. As a result, decreases in organ weights and toxicities were observed in the male and female reproductive system, adrenal glands, liver, pituitary (rats only), and male mammary glands. The changes in the reproductive organs are consistent with the antiandrogenic pharmacological activity of abiraterone acetate.

13.2 Animal Toxicology and/or Pharmacology

Niraparib

In vitro, niraparib bound to DAT, NET, and SERT and inhibited uptake of norepinephrine and dopamine in cells with IC50 values that were lower than the Cmin at steady-state in patients receiving the 200 mg dose. Niraparib has the potential to cause effects in patients related to inhibition of these transporters (e.g., cardiovascular, central nervous system). Intravenous administration of niraparib to vagotomized dogs over 30 minutes at 1, 3, and 10 mg/kg resulted in an increased range of arterial pressures of 13% to 20%, 18% to 27%, and 19% to 25%, respectively, and increased range of heart rates of 2% to 11%, 4% to 17%, and 12% to 21%, respectively, above pre-dose levels. The unbound plasma concentrations of niraparib in dogs at these dose levels were approximately 1.2, 3.9, and 15.5 times the unbound Cmax at steady state in patients receiving the 200 mg dose.

In addition, niraparib crossed the blood-brain barrier in rats and monkeys following oral administration. The cerebrospinal fluid plasma Cmax ratios of niraparib administered at 10 mg/kg orally to two rhesus monkeys were 0.10 and 0.52.

Abiraterone Acetate

A dose-dependent increase in cataracts was observed in rats after daily oral abiraterone acetate administration for 26 weeks starting at ≥50 mg/kg/day (similar to the human clinical exposure (AUC) at 1,000 mg dose daily). In a 39-week monkey study with daily oral abiraterone acetate administration, no cataracts were observed at higher doses (2 times greater than the clinical exposure (AUC) at 1,000 mg dose daily).

14 CLINICAL STUDIES

14.1 BRCA2-mutated Metastatic Castration-Sensitive Prostate Cancer (mCSPC)

The efficacy of AKEEGA was investigated in AMPLITUDE (NCT04497844), a randomized double-blind, placebo-controlled, multi-cohort, multi-center study in which 696 patients with homologous recombination repair (HRR) gene-mutated (HRRm) mCSPC were randomized (1:1) to receive niraparib 200 mg and abiraterone acetate 1,000 mg (N=348) or placebo and abiraterone acetate (N=348). All patients received prednisone 5 mg daily and were required to have androgen deprivation therapy (ADT) (medical or surgical) >14 days prior to randomization. The only allowable prior systemic therapy in the mCSPC setting, was up to 45 days of abiraterone acetate, up to 6 cycles of docetaxel, and up to 6 months of ADT.

Randomization was stratified by HRR gene alteration (BRCA2versus CDK12versus all other pathogenic alterations), prior docetaxel use (yes versus no), and volume of disease at screening (high versus low).

Of the 696 patients enrolled, 323 were randomized as having BRCA2gene mutation (BRCA2m). Mutation status was determined prospectively using the Foundation One CDx tissue assay or other clinical trial assays.

Among the 323 patients with BRCA2m the median age was 66 years (range 41; 92); 68% were White, 25% Asian, 4% Black, and 3% other or not reported; 10% were Hispanic or Latino; and baseline ECOG performance status was 0 (68%), 1 (30%) or 2 (1.2%). 16% had received prior docetaxel and 11% received prior abiraterone acetate for up to 45 days for mCSPC. 40% had bone-only metastases and 15% had visceral metastases, 10% had BRCA2 mutations in combination with mutations in other HRR genes.

The major efficacy outcome measure was radiographic progression free survival (rPFS) determined by investigator-assessed radiographic progression by bone scan (according to PCWG3 criteria) or soft tissue lesions by CT or MRI (according to RECIST 1.1 criteria) or death, whichever occurred first. Overall Survival (OS) and Time to Symptomatic Progression (TSP) were additional efficacy outcome measures. A statistically significant improvement in rPFS for niraparib and abiraterone acetate compared to placebo and abiraterone acetate was observed in the overall population of patients with HRRm. In an exploratory analysis in the subgroup of 373 patients with non- BRCA2mutations, the investigator-assessed rPFS hazard ratio was 0.88 (95% CI: 0.63, 1.24), indicating that the improvement in the overall population was primarily attributed to the results seen in the subgroup of patients with BRCA2mutation.

The efficacy results are presented in Table 6 and Figure 1 for patients with BRCA2mutations in AMPLITUDE.

Table 6: Efficacy Results from the BRCA2m Subgroup of the AMPLITUDE Study
Endpoints | AKEEGA (N=162) | Placebo +Abiraterone Acetate (N=161)
Radiographic Progression-free Survival [Investigator-assessed]
Events | 48 (30%) | 82(51%)
Median (95% CI) time to event (months) | NE (41, NE) | 26 (18, 28)
Hazard Ratio (95% CI) [Calculated using an unstratified Cox proportional hazards model] | 0.46 (0.32, 0.66)
NE = not estimable

At the first interim analysis for OS, 91 deaths occurred in the BRCA2m population, 36 [22%] in the AKEEGA arm) and 55 [34%] in the placebo and abiraterone acetate arm.

Figure 1: Kaplan-Meier Plot of Radiographic Progression-Free Survival in the BRCA2m Population (AMPLITUDE)

Treatment with AKEEGA resulted in a delay in TSP (HR = 0.41, 95% CI= 0.26, 0.65). TSP was defined as the time from randomization to the time of symptomatic progression, which included use of external beam radiation for skeletal or pelvic symptoms, cancer-related morbid events, initiation of new systemic anti-cancer therapy, and other cancer-related procedures.

14.2 BRCA-mutated Metastatic Castration-Resistant Prostate Cancer (mCRPC)

The efficacy of AKEEGA was investigated in Cohort 1 of MAGNITUDE (NCT03748641), a randomized double-blind, placebo-controlled, multi-cohort, multi-center study in which 423 patients with homologous recombination repair (HRR) gene-mutated (HRRm) mCRPC were randomized (1:1) to receive niraparib 200 mg and abiraterone 1,000 mg (N=212) or placebo and abiraterone (N=211) until unacceptable toxicity or progression. All patients received prednisone 10 mg daily and a GnRH analog or had prior bilateral orchiectomy. Patients with mCRPC who had not received prior systemic therapy in the mCRPC setting except for a short duration of prior abiraterone acetate plus prednisone (up to four months) and ongoing ADT, were eligible. Patients could have received prior docetaxel or androgen-receptor (AR) targeted therapies in either the metastatic castration-sensitive prostate cancer (mCSPC) or non-metastatic castration-resistant prostate cancer (nmCRPC) setting.

Randomization was stratified by prior docetaxel for mCSPC (yes or no), prior AR targeted therapy for mCSPC or nmCRPC (yes or no), prior abiraterone acetate for mCRPC (yes or no), and BRCA-status (BRCAm vs. other).

Of the 423 patients enrolled, 225 (53%) had BRCA gene mutations (BRCA m). Mutation status of BRCA genes was determined prospectively using the Foundation One CDx tissue assay or other clinical trial assays.

Among the 225 patients with BRCA m, the median age was 68 years (range 43–100) and 66% were 65 years of age or older; 72% were White, 17% Asian, and 1% Black, and 10% other or not reported; 12% were Hispanic or Latino; and baseline ECOG performance status (PS) was 0 (66%) or 1 (34%). Twenty-four percent had received prior docetaxel, 5% received prior AR-targeted therapy for mCSPC or nmCRPC, and 26% received prior abiraterone acetate plus prednisone for up to 4 months for mCRPC. Thirty-seven percent had bone-only metastases and 21% had visceral metastases. Seven percent had BRCA1 mutations, 78% had BRCA2 mutations, and 15% had BRCA mutations in combination with mutations in other HRR genes.

The major efficacy outcome measure was radiographic progression free survival (rPFS) determined by blinded independent central radiology (BICR) review evaluated per Response Evaluation Criteria In Solid Tumors (RECIST) 1.1 (soft tissue lesions) and Prostate Cancer Working Group-3 (PCWG-3) criteria (bone lesions). Overall survival (OS) was an additional efficacy outcome measure.

A statistically significant improvement in rPFS for niraparib plus abiraterone compared to placebo plus abiraterone was observed in BRCA m patients, and the Cohort 1 intention to treat (ITT) population. In an exploratory analysis in the subgroup of 198 (47%) patients with non- BRCA mutations, the rPFS hazard ratio was 0.99 (95% CI: 0.67, 1.44) and the OS hazard ratio was 1.13 (95% CI: 0.77, 1.64), indicating that the improvement in the ITT population was primarily attributed to the results seen in the subgroup of patients with BRCA m.

The efficacy results are presented in Table 7 and Figures 2 and 3 for patients in Cohort 1 with BRCA mutations.

Table 7: Efficacy Results from the BRCAm Subgroup of the MAGNITUDE Study
Endpoints | AKEEGA (N=113) | Placebo + Abiraterone Acetate (N=112)
Radiographic Progression-free Survival [rPFS results based on blinded independent central review at primary analysis.]
Event of disease progression or death (%) | 45 (40%) | 64 (57%)
Median, months (95% CI) | 16.6 (13.9, NE) | 10.9 (8.3, 13.8)
Hazard Ratio [Cox proportional hazards model stratified by prior docetaxel (yes vs. no) and prior abiraterone (yes vs. no).] (95% CI) | 0.53 (0.36, 0.79)
p-value [Stratified log-rank test two-sided p-value] | 0.0014
NE = not estimable

At the protocol pre-specified final OS analysis in Cohort 1, 60 (53%) deaths and 70 (63%) deaths were observed in the AKEEGA arm and placebo arm, respectively, for patients with BRCAm. In an exploratory OS analysis in the subgroup of patients with BRCAm, the median in the AKEEGA arm was 30.4 (95% CI: 27.6, NE) and 28.6 months (95% CI: 23.8, 33.0) in the placebo arm, with an OS hazard ratio of 0.79 (95% CI: 0.55, 1.12).

Figure 2: Kaplan-Meier Plot of BICR Assessed Radiographic Progression-Free Survival in the BRCAm Population (MAGNITUDE, primary analysis)

Figure 3: Kaplan-Meier Plot of Overall Survival in the BRCAm Population (MAGNITUDE, final analysis)

16 HOW SUPPLIED/STORAGE AND HANDLING

AKEEGA® (niraparib and abiraterone acetate) tablets are available in the strengths and packages listed below:

- AKEEGA 50 mg/500 mg film-coated tablets
  Yellowish orange to yellowish brown, oval, film-coated tablets debossed with "N 50 A" on one side and plain on the other side. They are available in bottles of 60 tablets.
  NDC 57894-050-60
- AKEEGA 100 mg/500 mg film-coated tablets
  Orange, oval, film-coated tablets debossed with "N 100 A" on one side and plain on the other side. They are available in bottles of 60 tablets.
  NDC 57894-100-60

Storage and Handling

Store at 20°C to 25°C (68°F to 77°F); excursions permitted to 15°C to 30°C (59°F to 86°F) [see USP Controlled Room Temperature].

Based on its mechanism of action, AKEEGA may harm a developing fetus. Females who are or may become pregnant should handle AKEEGA tablets with protection, e.g., gloves [see Use in Specific Populations (8.1)] .

17 PATIENT COUNSELING INFORMATION

Advise the patient to read the FDA-approved patient labeling (Patient Information).

Hematologic Adverse Reactions

- Advise patients that periodic monitoring of their blood counts is recommended. Advise patients to contact their healthcare provider for new onset of pallor, weakness, dyspnea, fatigue, bleeding, fever, or symptoms of infection [see Warnings and Precautions (5.1, 5.2)] .

Hypokalemia, Fluid Retention, and Cardiovascular Adverse Reactions

- Inform patients that AKEEGA is associated with, hypokalemia that may lead to QT prolongation. Advise patients that hypertension, hypokalemia, and fluid retention will be monitored at least weekly for the first two months, then once a month. Advise patients to adhere to corticosteroids and to report symptoms of hypokalemia or edema to their healthcare provider [see Warnings and Precautions (5.3)] .

Hepatotoxicity and Hepatic Impairment

- Inform patients that AKEEGA is associated with severe hepatotoxicity. Inform patients that their liver function will be monitored using blood tests. Advise patients to immediately report symptoms of hepatotoxicity to their healthcare provider [see Warnings and Precautions (5.4)] .

Adrenocortical Insufficiency

- Inform patients that AKEEGA with prednisone is associated with adrenal insufficiency. Advise patients to report symptoms of adrenocortical insufficiency to their healthcare provider [see Warnings and Precautions (5.5)] .

Hypoglycemia

- Inform patients that AKEEGA is associated with hypoglycemia. Advise patients with diabetes to monitor blood glucose during and after discontinuation of treatment with AKEEGA [see Warnings and Precautions (5.6)] .

Posterior Reversible Encephalopathy Syndrome

- Inform patients that they are at risk of developing posterior reversible encephalopathy syndrome (PRES) that can present with signs and symptoms including seizure, headaches, altered mental status, or vision changes. Advise patients to contact their healthcare provider if they develop any of these signs or symptoms [see Warnings and Precautions (5.8)] .

Dosage and Administration

- Inform patients that AKEEGA is taken orally once daily with prednisone daily (according to their healthcare provider's instructions) and to not interrupt or stop either of these medications without consulting their healthcare provider [see Dosage and Administration (2.2)] .
- Inform patients coadministered a gonadotropin-releasing hormone (GnRH) analog therapy that they need to maintain this treatment during the course of treatment with AKEEGA [see Dosage and Administration (2.2)] .
- Inform patients that in the event of a missed daily dose of AKEEGA, they should take their normal dose as soon as possible on the same day and resume their next dose at the normal schedule on the following day. The patient should not take extra tablets to make up the missed dose [see Dosage and Administration (2.2)] .
- Instruct patients to take AKEEGA tablets as a single dose once daily on an empty stomach. Instruct patients to take AKEEGA on an empty stomach at least one hour before or two hours after food. AKEEGA taken with food causes increased exposure and may result in adverse reactions. Instruct patients to swallow tablets whole with water and not to break, crush, or chew the tablets [see Dosage and Administration (2.2)] .

Embryo-Fetal Toxicity

- Inform patients that AKEEGA may harm a developing fetus and can cause loss of pregnancy [see Warnings and Precautions (5.9)and Use in Specific Populations (8.1)] .
- Advise males with female partners of reproductive potential to use effective contraception during treatment and for 4 months after the last dose of AKEEGA [see Use in Specific Populations (8.3)] .
- Advise females who are pregnant or may become pregnant to handle AKEEGA tablets with protection, e.g., gloves [see Use in Specific Populations (8.1)and How Supplied/Storage and Handling (16)] .

Infertility

- Advise male patients that AKEEGA may impair fertility [see Use in Specific Populations (8.3)].

Product of France

Manufactured for:
Janssen Biotech, Inc.
Horsham, PA 19044, USA

For patent information: www.janssenpatents.com

© Johnson & Johnson and its affiliates 2025

PATIENT INFORMATION
AKEEGA® (a kee' gah)
(niraparib and abiraterone acetate)
tablets

What is the most important information I should know about AKEEGA?
AKEEGA may cause serious side effects including:

- Bone marrow problems called myelodysplastic syndrome (MDS) or a type of cancer of the blood called acute myeloid leukemia (AML).MDS or AML that may lead to death has happened in people treated with AKEEGA. If you develop MDS or AML, your healthcare provider will stop treatment with AKEEGA.
  Symptoms of low blood cell counts (low red blood cells, low white blood cells, and low platelets) are common during treatment with AKEEGA but can also be a sign of serious bone marrow problems, including MDS and AML. Tell your healthcare provider if you have any of the following symptoms during treatment with AKEEGA:

- pale skin
- weakness
- shortness of breath
- feeling tired
- bruising or bleeding more easily

- fever
- frequent infections
- blood in urine or stool
- weight loss

Your healthcare provider will do blood tests to check your blood cell counts:

- weekly during the first month of treatment,
- every 2 weeks for the next 2 months of treatment,
- monthly for the remainder of the year,
- then every other month and as needed during treatment with AKEEGA.

See " What are the possible side effects of AKEEGA?" for more information about side effects.

What is AKEEGA?
AKEEGA is a prescription medicine used with prednisone to treat adults with prostate cancer:

- who have a certain type of abnormal BRCA gene, and
- whose prostate cancer has spread to other parts of the body (metastatic prostate cancer).

Your healthcare provider will perform a test to make sure AKEEGA is right for you.
It is not known if AKEEGA is safe and effective in females.
It is not known if AKEEGA is safe and effective in children.

Before taking AKEEGA, tell your healthcare provider about all of your medical conditions, including if you:

- have high blood pressure or heart problems
- have low blood potassium levels
- have liver or kidney problems
- have a history of adrenal problems
- have diabetes
- are receiving any other treatment for prostate cancer
- are pregnant or plan to become pregnant. AKEEGA can cause harm to your unborn baby and loss of pregnancy (miscarriage). Females who are or may become pregnant should handle AKEEGA tablets with protection, such as gloves.
- have a partner who is pregnant or may become pregnant.
  - Males with female partners who are able to become pregnant should use effective birth control (contraception) during treatment and for 4 months after the last dose of AKEEGA.
- are breastfeeding or plan to breastfeed. It is not known if AKEEGA passes into your breastmilk.

Tell your healthcare provider about all the medicines you take, including prescription and over-the-counter medicines, vitamins, and herbal supplements. AKEEGA may affect the way other medicines work, and other medicines may affect how AKEEGA works.

How should I take AKEEGA?

- Take AKEEGA and prednisone exactly as your healthcare provider tells you.
- Your healthcare provider may change your dose, temporarily stop, or permanently stop treatment with AKEEGA if you have certain side effects.
- Do not change or stop taking your prescribed dose of AKEEGA or prednisone without talking with your healthcare provider first.
- Take your prescribed dose of AKEEGA 1 time a day.
- Take AKEEGA on an empty stomach at least 1 hour before or 2 hours after food. Taking AKEEGA with food may cause more of the medicine to be absorbed by the body than is needed and this may cause side effects.
- Swallow AKEEGA tablets whole with water. Do not break, crush, or chew tablets.
- If you miss a dose of AKEEGA, take the dose as soon as possible on the same day. Return to your normal schedule on the following day. Do not take extra tablets to make up the missed dose.
- You should start or continue a gonadotropin-releasing hormone (GnRH) analog therapy during your treatment with AKEEGA unless you have had a surgery to lower the amount of testosterone in your body (surgical castration).
- If you take too much AKEEGA, call your healthcare provider or go to the nearest hospital emergency room right away.

What are the possible side effects of AKEEGA?
AKEEGA may cause serious side effects, including:

- See " What is the most important information I should know about AKEEGA?"
- Low blood potassium levels (hypokalemia), fluid retention (edema), high blood pressure (hypertension) and heart problems. To decrease the chance of this happening, you must take prednisone with AKEEGA exactly as your healthcare provider tells you. Your healthcare provider will check your blood pressure, do blood tests to check your potassium levels, and check for any signs and symptoms of fluid retention at least weekly for the first 2 months of treatment, then 1 time a month during treatment with AKEEGA. Tell your healthcare provider if you have any of the following symptoms:

- dizziness
- fast or irregular heartbeats
- feel faint or lightheaded
- headache

- confusion
- muscle weakness
- pain in your legs
- swelling in your hands, ankles, legs or feet

- Liver problems. Severe liver problems, liver failure and death has happened in people treated with abiraterone acetate, one of the medicines in AKEEGA. Your healthcare provider will do blood tests to check your liver function before starting treatment with AKEEGA, every 2 weeks for the first 3 months of treatment, and then monthly thereafter during treatment with AKEEGA. Tell your healthcare provider right away if you develop any symptoms of liver problems, including:

- yellowing of the skin or eyes
- darkening of the urine

- severe nausea or vomiting

- Adrenal problems. Adrenal problems may happen if you stop taking prednisone, get an infection, or are under stress. Tell your healthcare provider right away if you develop any symptoms of adrenal problems, including:

- feeling tired
- weakness
- feeling dizzy or lightheaded

- nausea or vomiting
- weight loss

- Low blood sugar (hypoglycemia).AKEEGA may cause low blood sugar in people taking medicines for diabetes. Severe low blood sugar has happened in people who take certain medicines for diabetes and were treated with abiraterone acetate, one of the medicines in AKEEGA. You and your healthcare provider should check your blood sugar levels during treatment and after you stop treatment with AKEEGA. Your healthcare provider may need to change the dose of your diabetes medicine to decrease your risk of low blood sugar. Tell your healthcare provider right away if you have any of the following signs or symptoms of low blood sugar, including:

- headache
- drowsiness
- weakness
- dizziness
- confusion

- irritability
- hunger
- fast heartbeat
- sweating
- feeling jittery

- Increased risk of bone fracture and death when abiraterone acetate, one of the medicines in AKEEGA, and prednisone or prednisolone is used in combination with a type of radiation called Radium 223 (Ra-223) dichloride. You should not receive treatment with Ra-223 dichloride for at least 5 days after your last dose of AKEEGA with prednisone. Tell your healthcare provider about any other treatments you are taking for prostate cancer.
- Posterior Reversible Encephalopathy Syndrome (PRES). PRES is a condition that affects the brain and may happen during treatment with AKEEGA. If you have headache, vision changes, confusion, or seizure with or without high blood pressure, please contact your healthcare provider.

The most common side effects of AKEEGA include:

- decreased hemoglobin
- decreased lymphocytes
- muscle and bone pain
- tiredness
- decreased platelets
- changes in liver function blood tests

- constipation
- high blood pressure
- nausea
- decreased neutrophils
- changes in kidney function blood tests
- increased potassium level in the blood

- decreased potassium level in the blood
- swelling in your legs or feet
- increased bilirubin levels in the blood
- respiratory tract infection
- irregular heartbeat (arrhythmia)

AKEEGA may cause fertility problems in males, which may affect the ability to father children. Talk to your healthcare provider if you have concerns about fertility.
These are not all the possible side effects of AKEEGA.
Call your doctor for medical advice about side effects. You may report side effects to FDA at 1-800-FDA-1088.

How should I store AKEEGA?

- Store AKEEGA at room temperature between 68°F to 77°F (20°C to 25°C).

Keep AKEEGA and all medicines out of the reach of children.

General information about the safe and effective use of AKEEGA.
Medicines are sometimes prescribed for purposes other than those listed in a Patient Information leaflet. Do not use AKEEGA for a condition for which it was not prescribed. Do not give AKEEGA to other people, even if they have the same symptoms that you have. It may harm them. You can ask your healthcare provider or pharmacist for information about AKEEGA that is written for health professionals.

What are the ingredients in AKEEGA?
Active ingredients: niraparib tosylate and abiraterone acetate
Inactive ingredients:
Core tablet: colloidal anhydrous silica, crospovidone, hypromellose, lactose monohydrate, magnesium stearate, silicified microcrystalline cellulose, sodium lauryl sulfate.
50 mg/500 mg film-coated tablets: The film-coating contains iron oxide black, iron oxide red, iron oxide yellow, sodium lauryl sulphate, glycerol monocaprylocaprate, polyvinyl alcohol, talc, and titanium dioxide.
100 mg/500 mg film-coated tablets: The film-coating contains iron oxide red, iron oxide yellow, sodium lauryl sulphate, glycerol monocaprylocaprate, polyvinyl alcohol, talc, and titanium dioxide.
Manufactured for: Janssen Biotech, Inc., Horsham, PA 19044, USA
For patent information: www.janssenpatents.com
© Johnson & Johnson and its affiliates 2025
For more information, call Janssen Biotech, Inc. at 1-800-526-7736 (1-800-JANSSEN) or go to www.akeegahcp.com.

This Patient Information has been approved by the U.S. Food and Drug Administration.

Revised: 12/2025

PRINCIPAL DISPLAY PANEL - 100 mg / 500 mg Bottle Carton

NDC 57894-100-60

Tamper AREA

Akeega™
(niraparib and
abiraterone acetate)
tablets

100 mg / 500 mg

Warning: Women who are or may
be(come) pregnant should not
handle AKEEGA™ tablets
without protection, e.g., gloves
(See Prescribing Information).

Do not break, crush, or chew tablets

Rx only

60 film-coated tablets

janssen

PRINCIPAL DISPLAY PANEL - 50 mg / 500 mg Bottle Carton

NDC 57894-050-60

Tamper AREA

Akeega™
(niraparib and
abiraterone acetate)
tablets

50 mg / 500 mg

Warning: Women who are or may
be(come) pregnant should not
handle AKEEGA™ tablets
without protection, e.g., gloves
(See Prescribing Information).

Do not break, crush, or chew tablets

Rx only

60 film-coated tablets

janssen